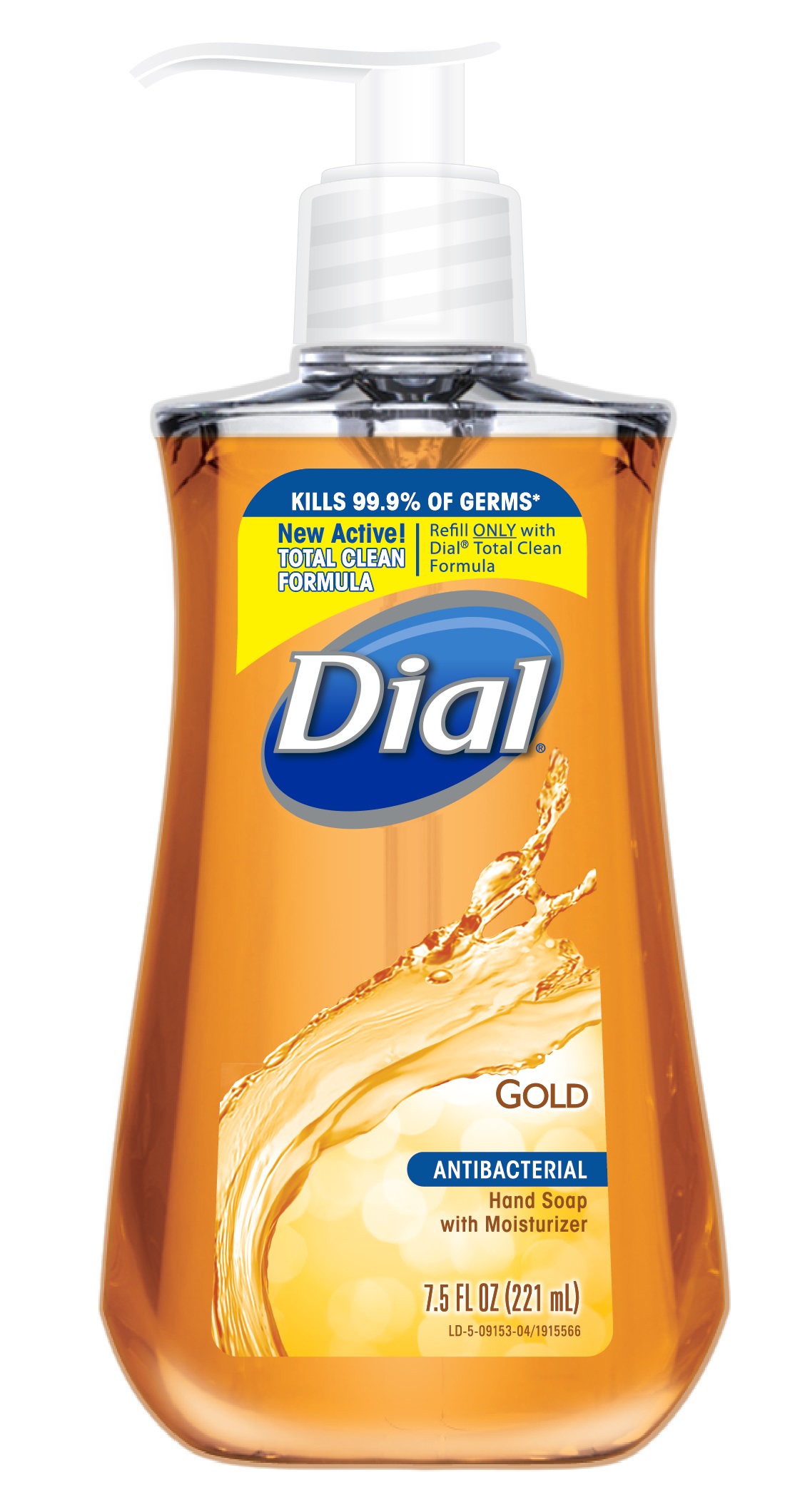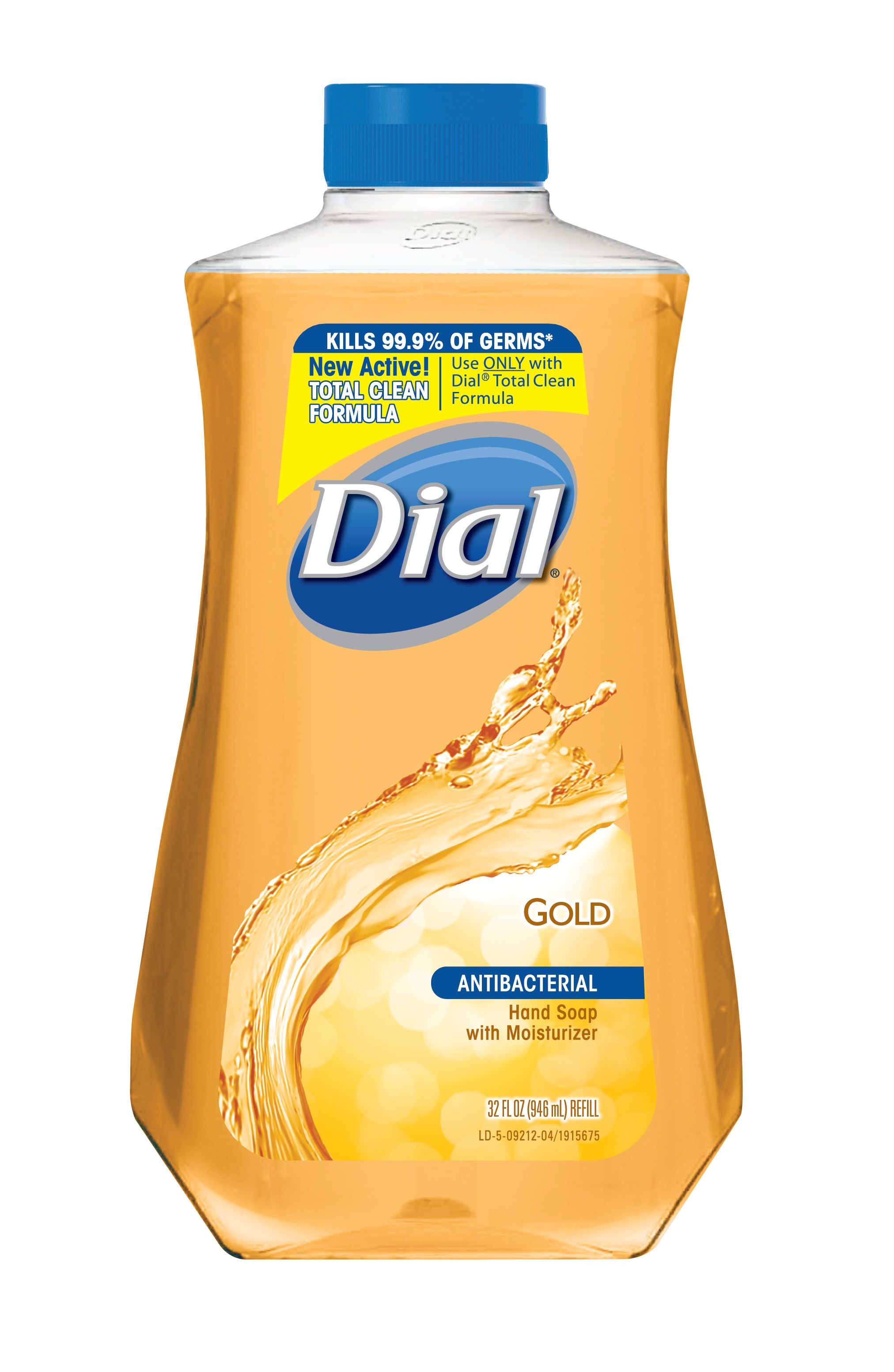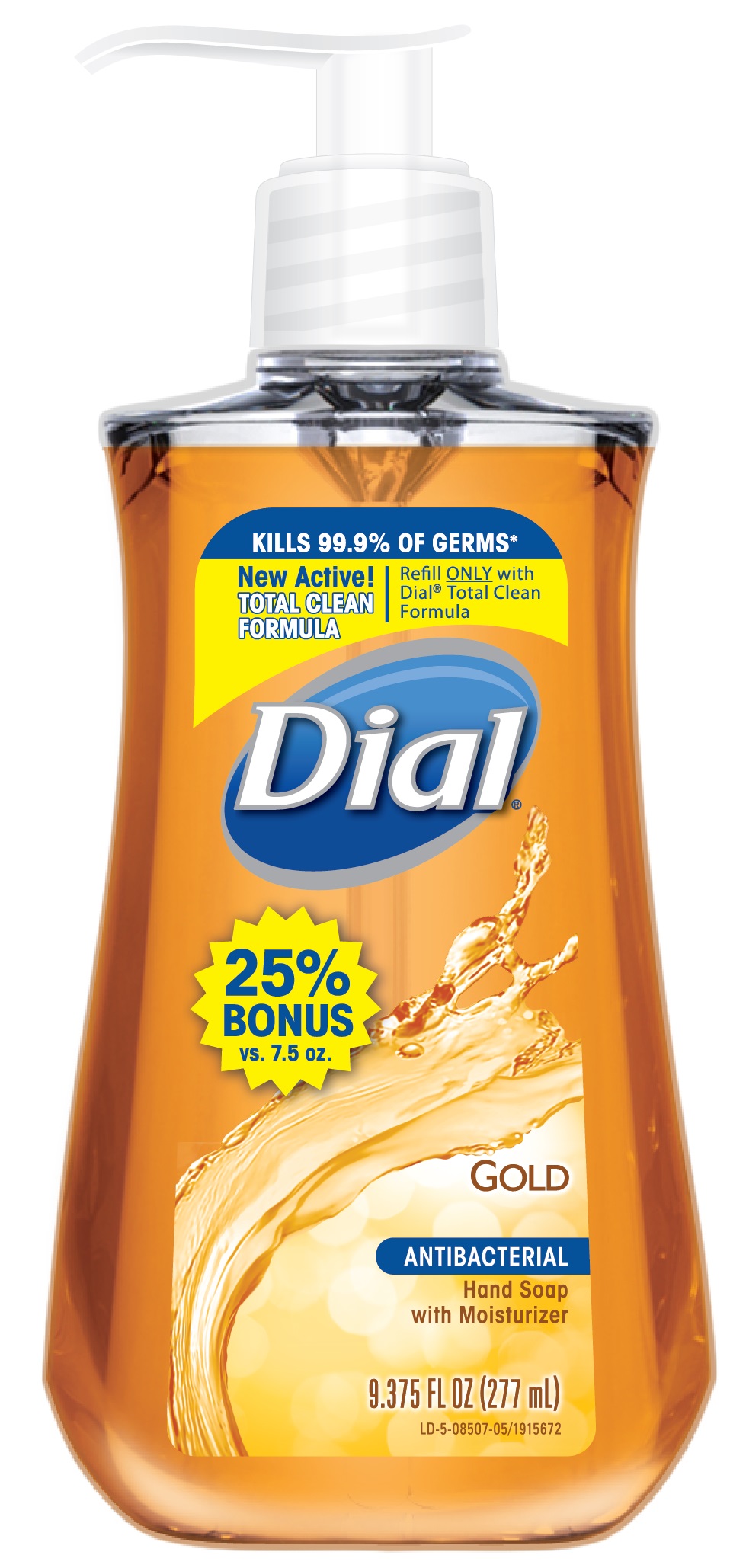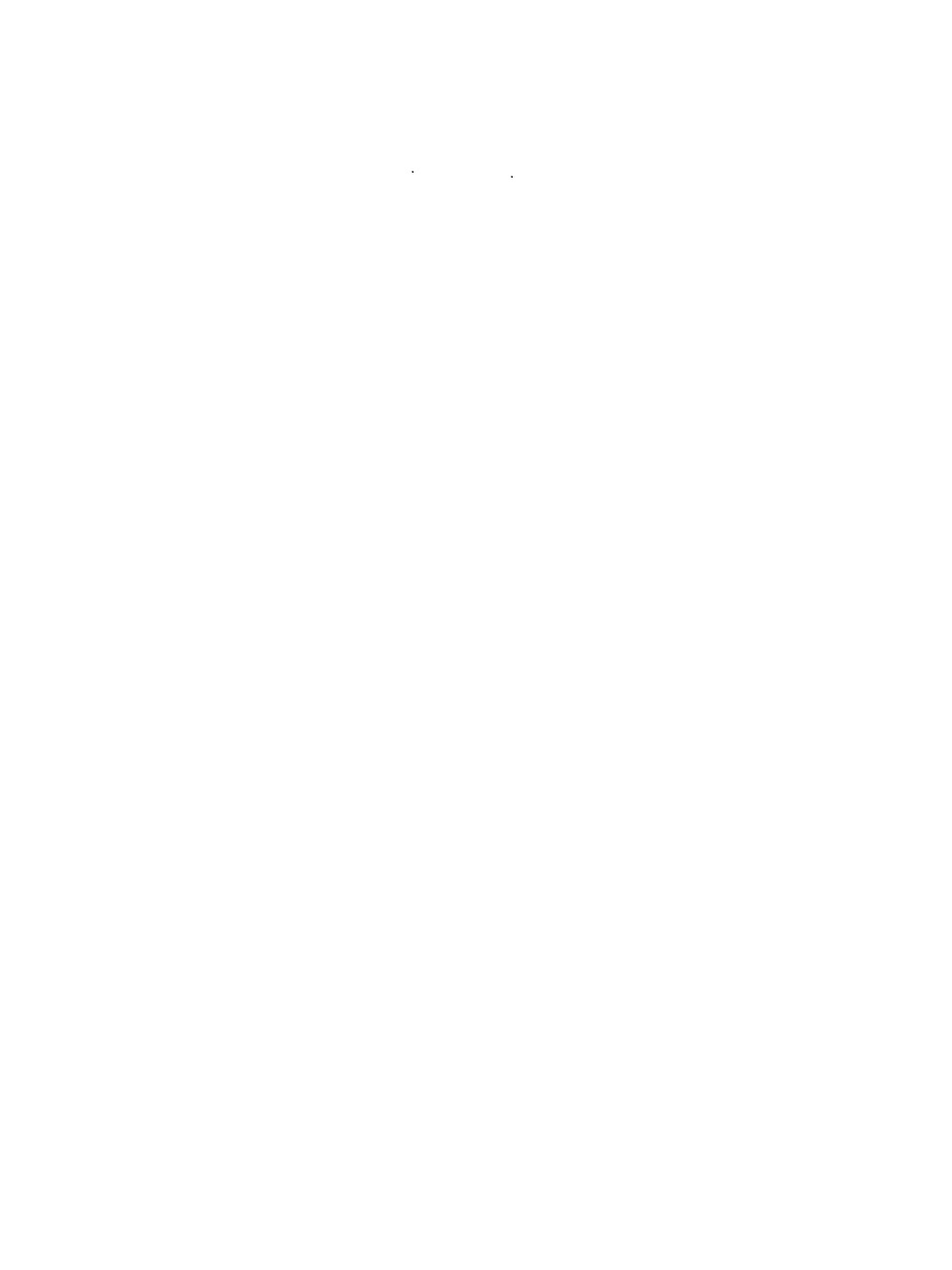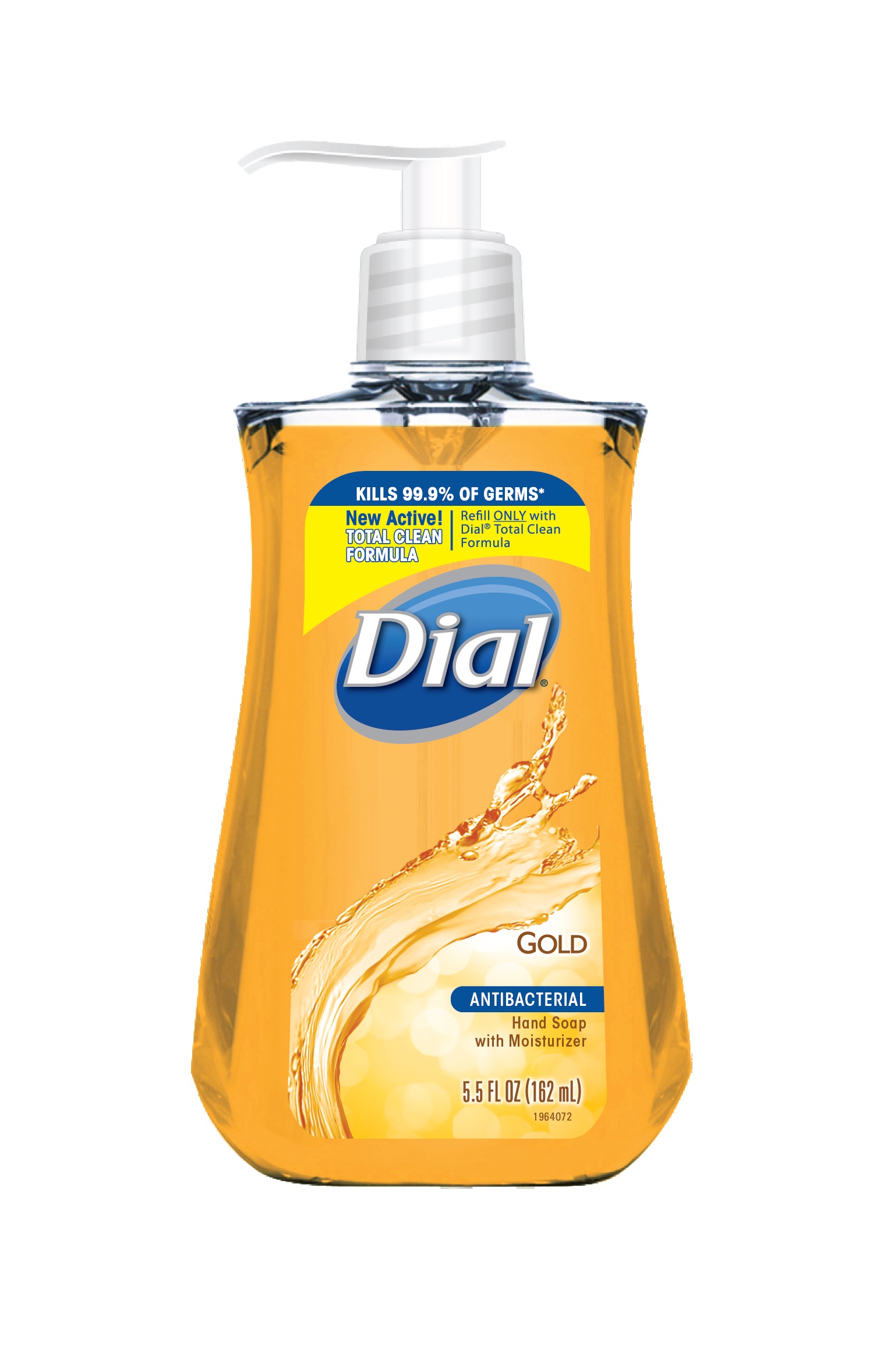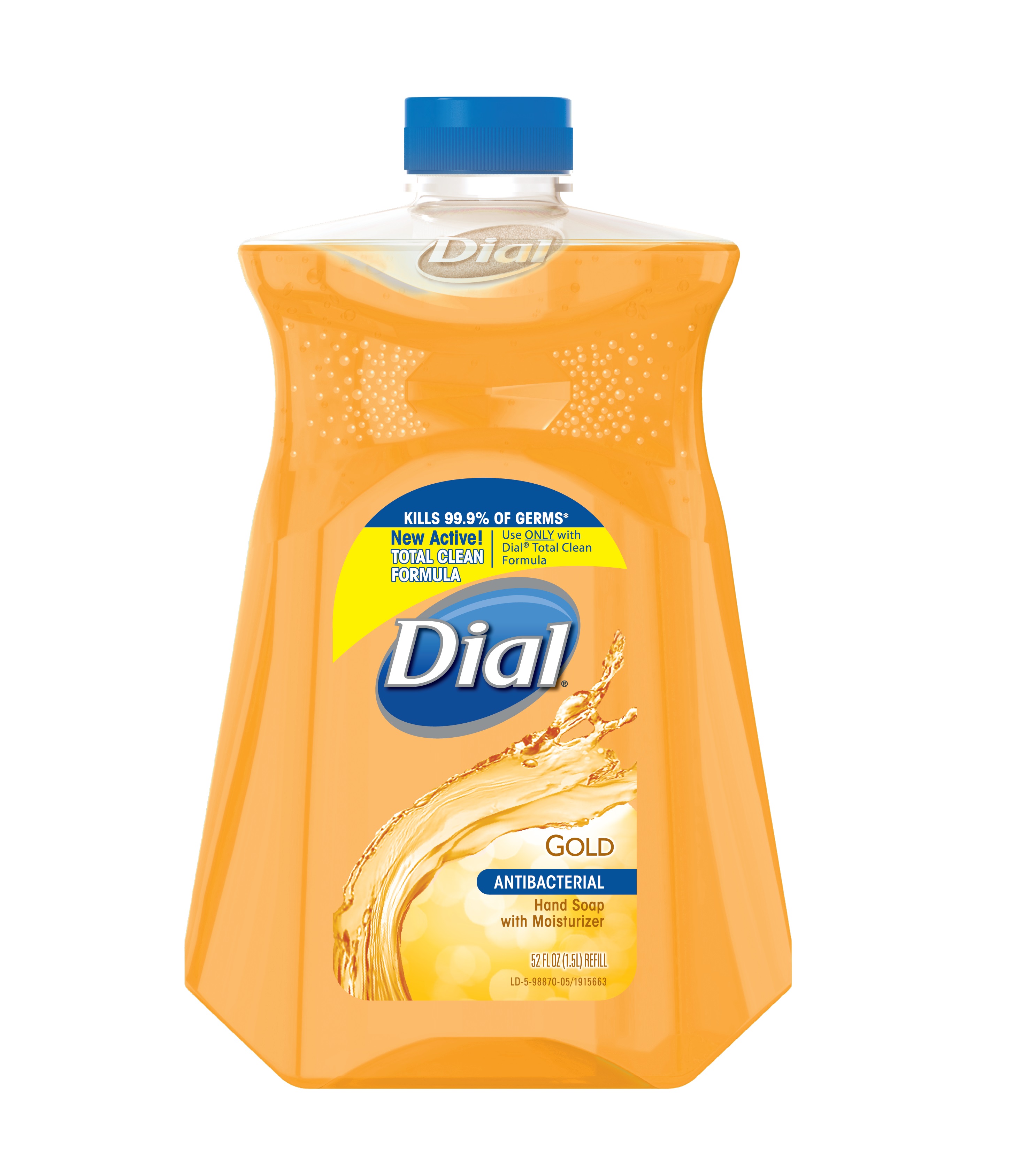 DRUG LABEL: Dial Antibacterial Hand Wash
NDC: 54340-243 | Form: SOLUTION
Manufacturer: The Dial Corporation, A Henkel Company
Category: otc | Type: HUMAN OTC DRUG LABEL
Date: 20141210

ACTIVE INGREDIENTS: Benzethonium Chloride .1 g/100 mL
INACTIVE INGREDIENTS: SODIUM CHLORIDE; FD&C YELLOW NO. 5; LAURAMINE OXIDE; COCO MONOETHANOLAMIDE; PEG-120 METHYL GLUCOSE DIOLEATE; GLYCERIN; EDETATE SODIUM; SODIUM BENZOATE; CITRIC ACID MONOHYDRATE; FD&C RED NO. 4; CETRIMONIUM CHLORIDE; LAURAMIDOPROPYLAMINE OXIDE

Dial Gold Antibacterial Hand Soap

Drug Facts

Active Ingredient

Benzethonium Chloride 0.1%

Purpose

Antibacterial

Uses

For handwashing to decrease bacteria on the skin

Warnings

For external use only

When using this product

Avoid contact with eyes. In case of eye contact, flush with water.

Stop use and ask a doctor if irritation and redness develops

Keep out of reach of children. If swallowed, get medical help or contact a
Poison Control Center right away.

Directions

pump into hands, wet as needed
lather vigorously for at least 15 seconds
wash skin, rinse thoroughly and dry

Inactive Ingredients

Inactive Ingredients: Water, Centrimonium Chloride, Glycerin, Lauramine Oxide,
Lauramidopropylamine Oxide, Sodium Chloride, Fragrance, PEG-120 Methyl Glucose Dioleate, Cocamide
MEA, Citric Acid, Sodium Benzoate, Tetrasodium EDTA, Yellow 5, Red 4

* Encountered in household settings

Questions

Questions? 1-800-258-DIAL (3425)

Visit our website at www.dialsoap.com MADE IN USA

©2014 & Distributed by THE DIAL CORPORATION
a Henkel COMPANY SCOTTSDALE, AZ 85255

The distinctive design and elements of this package are propriatary and
owned by The Dial Corporation, A Henkel Company

INDICATIONS AND USAGE

For handwashing to decrease bacteria on the skin

DOSAGE AND ADMINISTRATION

Topical Liquid

PACKAGE LABEL

Kills 99.9% of Germs*

New Active!
TOTAL CLEAN FORMULA

Refill ONLY with Dial© Total Clean Formula

DIAL
Gold
Hand Soap with Moisturizer
Antibacterial
7.5 FL OZ (221 mL)